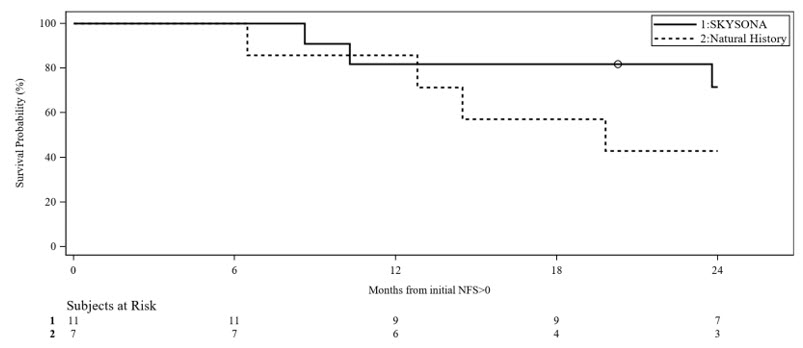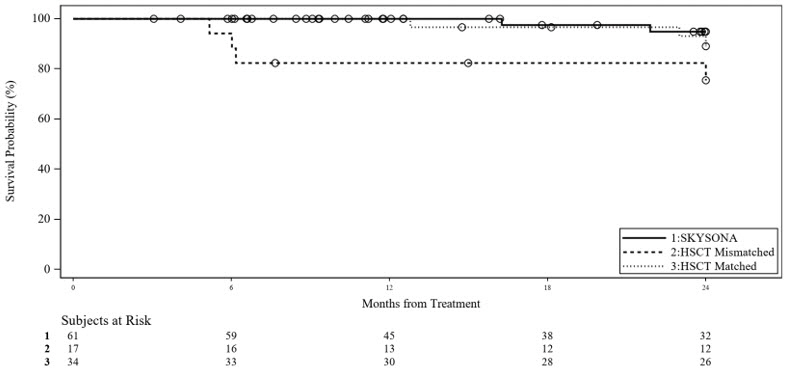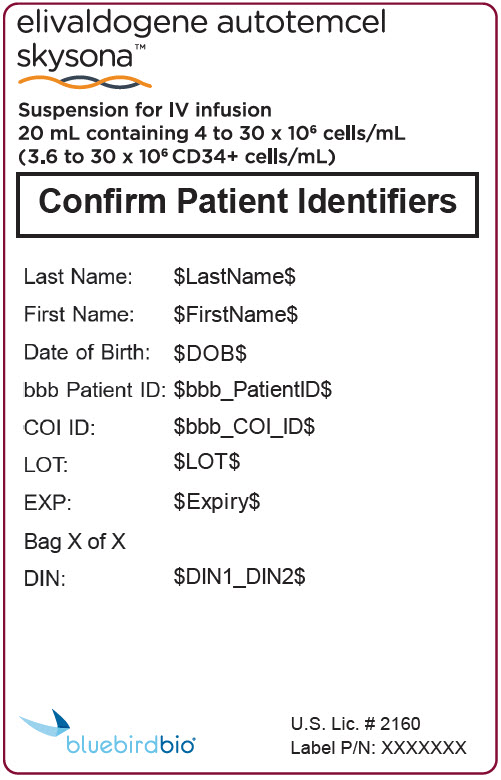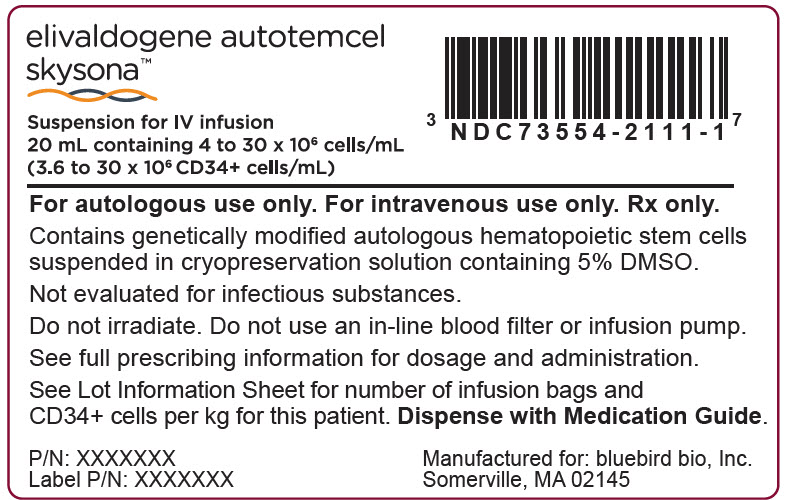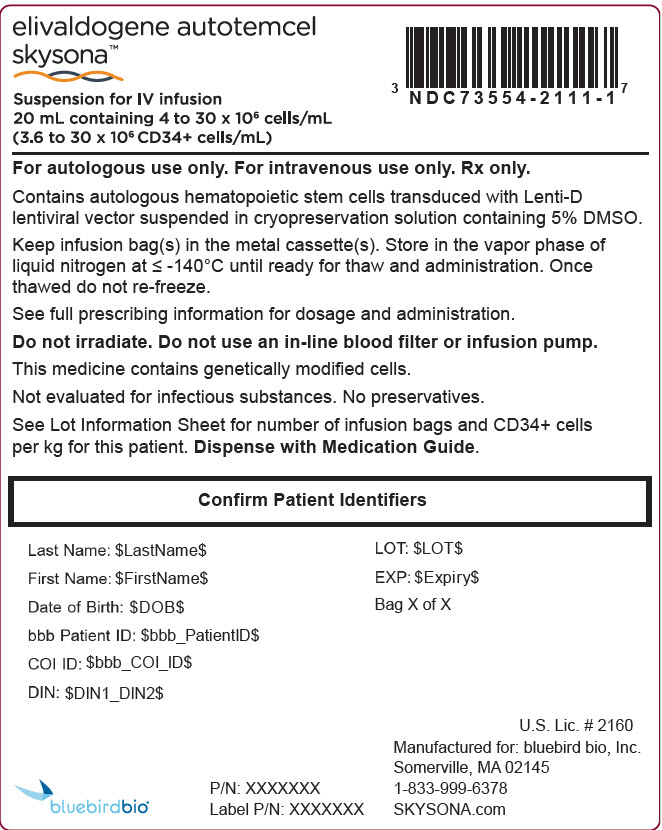 DRUG LABEL: Skysona
NDC: 73554-2111 | Form: SUSPENSION
Manufacturer: Genetix Biotherapeutics Inc.
Category: other | Type: CELLULAR THERAPY
Date: 20260126

ACTIVE INGREDIENTS: ELIVALDOGENE AUTOTEMCEL 30000000 1/1 1

HIGHLIGHTS OF PRESCRIBING INFORMATION

These highlights do not include all the information needed to use SKYSONA safely and effectively. See full prescribing information for SKYSONA.
SKYSONA® (elivaldogene autotemcel) suspension for intravenous infusion
Initial U.S. Approval: 2022

WARNING: HEMATOLOGIC MALIGNANCY

See full prescribing information for complete boxed warning.

Hematologic malignancies, including life-threatening cases of myelodysplastic syndrome and acute myeloid leukemia, have occurred in patients treated with SKYSONA. The cancers appear to be the result of treatment with SKYSONA. Monitor patients closely for evidence of malignancy through complete blood counts at least every 3 months and through assessments for evidence for clonal expansion or predominance at least twice in the first year and annually thereafter; consider bone marrow evaluations as clinically indicated. (5.1)

RECENT MAJOR CHANGES

Boxed Warning | 8/2025
Indications and Usage | 8/2025
Warnings and Precautions, Hematologic Malignancy (5.1) | 8/2025

1 INDICATIONS AND USAGE

SKYSONA is an autologous hematopoietic stem cell-based gene therapy indicated to slow the progression of neurologic dysfunction in boys 4-17 years of age with early, active cerebral adrenoleukodystrophy (CALD) without an available human leukocyte antigen (HLA)-matched donor for allogeneic hematopoietic stem cell transplant. Early, active CALD refers to asymptomatic or mildly symptomatic (neurologic function score, NFS ≤ 1) boys who have gadolinium enhancement on brain magnetic resonance imaging (MRI) and Loes scores of 0.5-9.

This indication is approved under accelerated approval based on 24-month Major Functional Disability (MFD)-free survival. [see Clinical Studies (14)]. Continued approval for this indication may be contingent upon verification and description of clinical benefit in a confirmatory trial(s). (1)

Limitations of Use

- SKYSONA does not treat or prevent adrenal insufficiency. (1)
- An immune response to SKYSONA may cause rapid loss of efficacy of SKYSONA in patients with full deletions of the human adenosine triphosphate binding cassette, sub family D, member 1 (ABCD1) gene. (1)
- SKYSONA has not been studied in CALD secondary to head trauma. (1)
- Given the risk of hematologic malignancy with SKYSONA, and unclear long-term durability of SKYSONA and human adrenoleukodystrophy protein (ALDP) expression, careful consideration should be given to the timing of treatment for each boy and treatment of boys with isolated pyramidal tract disease as clinical manifestations do not usually occur until adulthood. (1)

2 DOSAGE AND ADMINISTRATION

For autologous use only. For intravenous use only.

- Patients must undergo hematopoietic stem cell (HSC) mobilization and apheresis to obtain CD34+ cells for SKYSONA manufacturing. (2.2)
- Dosing of SKYSONA is based on the number of CD34+ cells in the infusion bag(s) per kg of body weight. (2.1)
- The minimum recommended dose is 5.0 × 10^6 CD34+ cells/kg. (2.1)
- Full myeloablative and lymphodepleting conditioning must be administered before infusion of SKYSONA. (2.2)
- Verify the patient's identity matches the unique patient identification information on the SKYSONA infusion bag(s) prior to infusion. (2.2)
- Do not sample, alter, or irradiate SKYSONA. (2.2)
- Do not use an in-line blood filter or an infusion pump. (2.3)

3 DOSAGE FORMS AND STRENGTHS

- SKYSONA is a cell suspension for intravenous infusion. (3)
- A single dose of SKYSONA contains a minimum of 5.0 × 10^6 CD34+ cells/kg of body weight, suspended in a solution containing 5% dimethyl sulfoxide (DMSO). (3)

4 CONTRAINDICATIONS

None. (4)

5 WARNINGS AND PRECAUTIONS

- Serious Infections: Life-threatening bacterial and viral infections may occur. Monitor patients for signs and symptoms of infection. (5.2)
- Prolonged Cytopenias: Patients may exhibit cytopenias >1 year after treatment. Monitor patients for bleeding and infection. (5.3)
- Delayed Platelet Engraftment: Monitor patients for thrombocytopenia and bleeding until platelet engraftment and count recovery. (5.4)
- Risk of Neutrophil Engraftment Failure: Monitor absolute neutrophil counts and if neutrophil engraftment does not occur, give rescue cells. (5.5)

6 ADVERSE REACTIONS

- Most common non-laboratory adverse reactions (≥ 20%): mucositis, nausea, vomiting, febrile neutropenia, alopecia, decreased appetite, abdominal pain, constipation, pyrexia, diarrhea, headache, rash. (6.1)
- Most common Grade 3 or 4 laboratory abnormalities (≥ 40%): leukopenia, lymphopenia, thrombocytopenia, neutropenia, anemia, hypokalemia. (6.1)

To report SUSPECTED ADVERSE REACTIONS, contact bluebird bio at 1-833-999-6378 or FDA at 1-800-FDA-1088 or www.fda.gov/medwatch.

7 DRUG INTERACTIONS

Anti-retrovirals: Do not take these medications from at least one month prior to starting mobilization agents until all cycles of apheresis are complete and after the expected duration of elimination. (7.2)

FULL PRESCRIBING INFORMATION

WARNING: HEMATOLOGIC MALIGNANCY

Hematologic malignancies, including life-threatening cases of myelodysplastic syndrome and acute myeloid leukemia, have occurred in patients treated with SKYSONA. Patients have been diagnosed between 14 months and 10 years after SKYSONA administration, and the cancers appear to be related to treatment with SKYSONA. Monitor patients closely for evidence of malignancy through complete blood counts at least every 3 months. Monitor patients through assessments for evidence for clonal expansion or predominance at least twice in the first year and annually thereafter; consider bone marrow evaluations as clinically indicated [see Warnings and Precautions (5.1)].

1 INDICATIONS AND USAGE

SKYSONA is indicated to slow the progression of neurologic dysfunction in boys 4-17 years of age with early, active cerebral adrenoleukodystrophy (CALD) without an available human leukocyte antigen (HLA)-matched donor for allogeneic hematopoietic stem cell transplant. Early, active cerebral adrenoleukodystrophy refers to asymptomatic or mildly symptomatic (neurologic function score, NFS ≤ 1) boys who have gadolinium enhancement on brain magnetic resonance imaging (MRI) and Loes scores of 0.5-9.

This indication is approved under accelerated approval based on 24-month Major Functional Disability (MFD)-free survival [see Clinical Studies (14)]. Continued approval for this indication may be contingent upon verification and description of clinical benefit in a confirmatory trial(s).

Limitations of Use

SKYSONA does not prevent the development of or treat adrenal insufficiency due to adrenoleukodystrophy.

An immune response to SKYSONA may limit the persistence of descendent cells of SKYSONA, causing rapid loss of efficacy of SKYSONA in patients with full deletions of the human adenosine triphosphate binding cassette, sub family D, member 1 (ABCD1) gene.

SKYSONA has not been studied in patients with CALD secondary to head trauma.

Given the risk of hematologic malignancy with SKYSONA, and unclear long-term durability of SKYSONA and human adrenoleukodystrophy protein (ALDP) expression, careful consideration should be given to the appropriateness and timing of treatment for each boy, especially for boys with isolated pyramidal tract disease since their clinical symptoms do not usually occur until adulthood.

2 DOSAGE AND ADMINISTRATION

For autologous use only. For intravenous use only.

2.1 Dose

SKYSONA is provided as a single dose for infusion containing a suspension of CD34+ cells in one or two infusion bags. The minimum recommended dose of SKYSONA is 5.0 × 10^6 CD34+ cells/kg.

The dose is calculated based on the patient's weight prior to first apheresis. See the Lot Information Sheet provided with the product shipment for additional information pertaining to dose.

2.2 Preparation Before SKYSONA Infusion

Before mobilization, apheresis, and conditioning are initiated, confirm that hematopoietic stem cell (HSC) transplantation is appropriate for the patient.

Perform screening for hepatitis B virus (HBV), hepatitis C virus (HCV), human immunodeficiency virus 1 & 2 (HIV-1/HIV-2) and Human T-lymphotropic virus 1 & 2 (HTLV-1/HTLV-2) in accordance with clinical guidelines before collection of cells for manufacturing.

Mobilization and Apheresis

Patients are required to undergo HSC mobilization followed by apheresis to obtain CD34+ cells for product manufacturing. Weigh the patient prior to the first apheresis collection. Collect a minimum number of CD34+ cells of 12 × 10^6 CD34+ cells/kg.

A back-up collection of CD34+ cells of ≥ 1.5 × 10^6 CD34+ cells/kg (if collected by apheresis) or ≥ 1.0 × 10^8 TNC/kg (Total Nucleated Cells, if collected by bone marrow harvest) is required. Collect and cryopreserve these cells prior to initiating conditioning and infusion with SKYSONA. The back-up collection may be needed for rescue treatment if there is: 1) compromise of SKYSONA after initiation of conditioning and before SKYSONA infusion, 2) primary engraftment failure, or 3) loss of engraftment after infusion with SKYSONA.

Myeloablative and Lymphodepleting Conditioning

Full myeloablative and lymphodepleting conditioning must be administered before infusion of SKYSONA. Consult prescribing information for the conditioning agents prior to treatment.

Do not begin conditioning until SKYSONA has been received and stored at the treatment center and the availability of the back-up collection of CD34+ cells is confirmed. After completion of conditioning, allow a minimum of 48 hours of washout before SKYSONA infusion.

Receipt and Storage of SKYSONA

- Ensure the availability of vapor phase of liquid nitrogen storage at less than or equal to -140°C (-220°F) at the treatment center.
- SKYSONA is shipped to the treatment center in the vapor phase of liquid nitrogen shipper.
- Confirm Patient Identifiers on the product labels and Lot Information Sheet within the shipper.
- If there are any concerns about the product or packaging upon receipt, contact bluebird bio at 1-833-999-6378.
- Keep the infusion bag(s) in the metal cassette(s) and transfer SKYSONA from the vapor phase of liquid nitrogen shipper to the treatment center vapor phase of liquid nitrogen storage at less than or equal to -140°C (-220°F) until ready for thaw and administration.

Preparation of SKYSONA for Infusion

Coordinate the timing of SKYSONA thaw and infusion. Confirm the infusion time in advance and adjust the start time of SKYSONA thaw such that it will be available for infusion when the patient and healthcare providers are ready.

SKYSONA contains human blood cells that are genetically modified with replication-incompetent, self-inactivating Lenti-D lentiviral vector (LVV). Follow universal precautions and local biosafety guidelines for handling and disposal of SKYSONA to avoid potential transmission of infectious diseases.

1. Remove each metal cassette from liquid nitrogen storage.
2. Confirm that SKYSONA is printed on the infusion bag(s) label(s).
3. Confirm that patient identity matches the unique patient identification information located on the SKYSONA infusion bag(s). Do not infuse SKYSONA if the information on the patient-specific label on the infusion bag does not match the intended patient, and contact bluebird bio at 1-833-999-6378.
4. A SKYSONA dose may be contained in one or two patient-specific infusion bags. Ensure that the correct number of infusion bags are present. Use the accompanying Lot Information Sheet to confirm that each infusion bag is within the expiration date prior to preparation of SKYSONA for infusion.
5. Remove the overwrap and inspect each infusion bag for any breaches of integrity before thawing and infusion. If an infusion bag is compromised, follow the local guidelines and contact bluebird bio immediately at 1-833-999-6378.
6. If more than one infusion bag is provided to achieve the treatment dose, thaw and administer each infusion bag completely before proceeding to thaw the next infusion bag. Maintain the second infusion bag, if applicable, within the cold-storage dewar to maintain temperature less than or equal to -140°C (-220°F) until time to thaw.
7. Thaw SKYSONA at 37°C (98.6°F) in a water bath or dry bath. Thawing of each infusion bag takes approximately 2 to 4 minutes. Promptly remove the infusion bag from the bath once thawed. Do not leave SKYSONA unattended and do not submerge the infusion ports if thawed in a water bath.
8. After thawing, mix SKYSONA gently by massaging the infusion bag to disperse clumps of cellular material until all of the contents are uniform. If visible cell clumps remain, continue to gently mix the contents of the bag. Most small clumps of cellular material should disperse with gentle manual mixing. Do not filter, wash, spin down and/or resuspend SKYSONA in new media prior to infusion.
9. Do not sample, alter, irradiate or refreeze SKYSONA.

2.3 Administration

SKYSONA is for autologous use only. The patient's identity must match the patient identifiers on the SKYSONA cassette(s) and infusion bag(s). Do not infuse SKYSONA if the information on the patient-specific label does not match the intended patient.

- Do not use an in-line blood filter or an infusion pump.

1. Before infusion, confirm that the patient's identity matches the unique patient identifiers on the SKYSONA infusion bag(s). The total number of infusion bags to be administered should also be confirmed with the Lot Information Sheet.
2. Prime the tubing of the infusion set with 0.9% sodium chloride solution prior to infusion.
3. Expose the sterile port on the infusion bag by tearing off the protective wrap covering the port.
4. Access the SKYSONA infusion bag and infuse per the treatment center's standard procedures for administration of cell therapy products.
5. Complete the infusion of SKYSONA as soon as possible, and no more than 4 hours after thawing.
6. Administer each infusion bag of SKYSONA via intravenous infusion (drip) by gravity flow over a period of less than 60 minutes.
7. After the entire content of the infusion bag is infused, flush all SKYSONA remaining in the infusion bag and any associated tubing with at least 50 mL of 0.9% sodium chloride solution to ensure that as many cells as possible are infused into the patient.
8. If more than one infusion bag is provided, administer each infusion bag completely before proceeding to thaw (following Section 2.2 steps 7-8) and infuse (following Section 2.3 steps 2-6) the next infusion bag.

After SKYSONA Administration

Standard procedures for patient management after HSC transplantation should be followed after SKYSONA infusion.

- Irradiate any blood products required within the first 3 months after SKYSONA infusion.
- Patients treated with SKYSONA should not donate blood, organs, tissues, or cells at any time in the future.

3 DOSAGE FORMS AND STRENGTHS

SKYSONA is a cell suspension for intravenous infusion.

SKYSONA is composed of one or two infusion bags which contain 4 to 30 × 10^6 cells/mL suspended in cryopreservation solution [see How Supplied/Storage and Handling (16)]. Each infusion bag contains approximately 20 mL of SKYSONA. A single dose of SKYSONA contains a minimum of 5.0 × 10^6 CD34+ cells per kg of body weight, suspended in cryopreservation solution.

See the Lot Information Sheet for actual dose.

4 CONTRAINDICATIONS

None.

5 WARNINGS AND PRECAUTIONS

5.1 Hematologic Malignancy

Hematologic malignancies, including myelodysplastic syndrome (MDS) and acute myeloid leukemia (AML), have developed in patients treated with SKYSONA in clinical studies between 14 months and 10 years after SKYSONA administration [see Adverse Reactions (6.1)]. Malignancies are life-threatening. Death related to treatment for malignancy and relapse of malignancy have occurred.

SKYSONA Lenti-D lentiviral vector genomic integration, including into the proto-oncogene MECOM, appears to have mediated the cases of hematologic malignancy. All patients treated with SKYSONA in clinical studies have integrations into MECOM; however, it is unknown which integrations into MECOM or other genes are likely to lead to malignancy.

Consider consultation with hematology experts prior to SKYSONA treatment to inform benefit-risk treatment decision and to ensure adequate monitoring for hematologic malignancy. Consider performing the following baseline hematologic assessments: complete blood count with differential, hematopathology review of peripheral blood smear, and bone marrow biopsy (core and aspirate) with flow cytometry, conventional karyotyping, and next generation sequencing (NGS) with a molecular panel appropriate for age and including coverage for gene mutations expected in myeloid and lymphoid malignancies; and testing for germline mutations that are associated with hematologic malignancy.

Early diagnosis of hematologic malignancy can be critically important, therefore, monitor patients treated with SKYSONA lifelong for hematologic malignancy. For at least the first fifteen years after treatment with SKYSONA, monitor via complete blood count (with differential) at least every 3 months and via integration site analysis or other testing for evidence of clonal expansion and predominance at least twice in the first year and then annually. Consider appropriate expert consultation and additional testing such as more frequent complete blood count (with differential) and integration site analysis, bone marrow studies, and gene expression studies in the following settings after treatment with SKYSONA:

- Delayed or failed engraftment of platelets or other cell lines (while all patients are at risk for hematologic malignancy, patients who do not achieve unsupported platelet counts of ≥ 20 × 10^9/L on or after Day 60 appear to be at higher risk); or
- New or prolonged cytopenias; or,
- Presence of clonal expansion or predominance (e.g., increasing relative frequency of an integration site, especially if ≥ 10% and present in MECOM or another proto-oncogene known to be involved in hematologic malignancy).

If hematologic malignancy is detected in a patient who received SKYSONA, contact bluebird bio at 1-833-999-6378 for reporting and to obtain instructions on collection of samples for further testing.

Post-Marketing Long Term Follow-Up Study

Patients who intend to receive treatment with SKYSONA are encouraged to enroll in the study, as available, to assess the long-term safety of SKYSONA and the risk of malignancies occurring after treatment with SKYSONA by calling bluebird bio, Inc. at 1-833-999-6378. The study includes monitoring (at pre-specified intervals) for clonal expansion.

5.2 Serious Infections

Severe infections, including life-threatening and fatal infections, have occurred in patients after SKYSONA infusion.

Febrile neutropenia was commonly observed in clinical studies and may be a sign of a serious infection. In the event of febrile neutropenia, evaluate for infection and manage with broad-spectrum antibiotics, fluids, and other supportive care as medically indicated.

Monitor patients for signs and symptoms of infection before and after SKYSONA administration and treat appropriately. Administer prophylactic antimicrobials according to best clinical practices and clinical guidelines.

Avoid administration of SKYSONA in patients with active infections.

5.3 Prolonged Cytopenias

Patients may exhibit cytopenias, including pancytopenia, for > 1 year following conditioning and SKYSONA infusion [see Adverse Reactions (6.1)].

Monitor blood counts until normalization and assess patients for signs and symptoms of bleeding and/or infection prior to and after SKYSONA administration.

5.4 Delayed Platelet Engraftment

Delayed platelet engraftment (platelet count ≤ 50 × 10^9/L beyond 60 days after treatment with SKYSONA) has been observed [see Adverse Reactions (6.1)]. Bleeding risk is increased prior to platelet engraftment and may continue after engraftment in patients with prolonged thrombocytopenia.

Patients should be made aware of the risk of bleeding until platelet recovery has been achieved. Monitor patients for thrombocytopenia and bleeding according to standard guidelines. Conduct frequent platelet counts until platelet engraftment and platelet recovery are achieved. Perform blood cell count determination and other appropriate testing whenever clinical symptoms suggestive of bleeding arise.

5.5 Risk of Neutrophil Engraftment Failure

There is a potential risk of neutrophil engraftment failure after treatment with SKYSONA. Neutrophil engraftment failure was defined as failure to achieve 3 consecutive absolute neutrophil counts (ANC) ≥ 0.5 × 10^9 cells/L obtained on different days by Day 43 after infusion of SKYSONA. Monitor neutrophil counts until engraftment has been achieved. If neutrophil engraftment failure occurs in a patient treated with SKYSONA, provide rescue treatment with the back-up collection of CD34+ cells [see Adverse Reactions (6.1)].

5.6 Hypersensitivity Reactions

Allergic reactions may occur with the infusion of SKYSONA. The dimethyl sulfoxide (DMSO) in SKYSONA may cause hypersensitivity reactions, including anaphylaxis which is potentially life-threatening and requires immediate intervention.

5.7 Anti-retroviral Use

Patients should not take anti-retroviral medications for at least one month prior to mobilization or the expected duration for elimination of the medications, and until all cycles of apheresis are completed. Anti-retroviral medications may interfere with manufacturing of the apheresed cells [see Drug Interactions (7.2)].

If a patient requires anti-retrovirals for HIV prophylaxis, mobilization and apheresis of CD34+ cells should be delayed until HIV infection is adequately ruled out.

5.8 Laboratory Test Interference

SKYSONA affects polymerase chain reaction (PCR) assays for HIV due to LVV provirus insertion. A PCR-based assay should not be used to screen for HIV infection in patients treated with SKYSONA as a false-positive test result is likely.

6 ADVERSE REACTIONS

6.1 Clinical Trials Experience

Because clinical trials are conducted under widely varying conditions, adverse reaction rates observed in the clinical trials of a drug cannot be directly compared to rates in the clinical trials of another drug and may not reflect the rates observed in practice.

The safety data described in this section reflect exposure to a single dose of SKYSONA in 67 patients with CALD. Data were obtained from two single-arm trials and, for 36 patients, from a long-term follow-up study [see Clinical Studies (14)]. The median (min, max) age across studies was 6 (4, 14) years; 100% were male; 54% were White/Caucasian, 4% were Black or African American, 1% were Asian, 10% were of other races including mixed race, and 30% did not report race; 25% were of Hispanic ethnicity. The median (min, max) duration of follow-up at time of initial approval was 24 (1, 88) months.

In the two trials, serious adverse reactions from Day 1 (SKYSONA infusion) to last follow-up occurred in 54% of patients. The most common non-laboratory, serious adverse reactions (≥ 3% incidence) that occurred after treatment with SKYSONA were febrile neutropenia (18%), pyrexia (fever) (18%), seizure (7%), myelodysplastic syndrome (4%), pseudomonal bacteremia (3%), pancytopenia (3%), vascular device infection (3%), mucositis (3%), and vomiting (3%).

Most common non-laboratory adverse reactions by time of onset follow:

- During mobilization and conditioning and occurring in ≥ 20% of patients: nausea (79%), vomiting (72%), decreased appetite (42%), catheter site pain (39%), constipation (30%), headache (24%), abdominal pain (21%), rash (13%)
- In the first 60 days after treatment with SKYSONA in ≥ 15% of patients: mucositis (88%), febrile neutropenia (73%), alopecia (72%), abdominal pain (33%), vomiting (31%), decreased appetite (31%), pyrexia (27%), nausea (27%), constipation (21%), diarrhea (21%), epistaxis (19%), pruritus (18%), headache (16%), oropharyngeal pain (16%), skin hyperpigmentation (16%), anxiety (15%)
- Between 60 days and 1 year after treatment with SKYSONA in ≥ 5% of patients: pyrexia (fever) (9%) and vomiting (6%)

Table 1 presents non-laboratory adverse reactions reported in at least 10% of patients between the start of conditioning and 24 months after SKYSONA administration. Table 2 presents Grade 3 or 4 laboratory abnormalities that occurred in at least 40% of patients between the start of conditioning and 24 months after SKYSONA administration.

Table 1: Non-Laboratory Adverse Reactions Reported in ≥ 10% of Patients Between the Start of Conditioning and 24 Months Following Treatment with SKYSONA [Includes adverse events associated with conditioning.]
Adverse Reaction | Any Grade n (%) | Grade 3 or Higher n (%)
Blood and lymphatic system disorders | -- | --
Febrile neutropenia [Febrile neutropenia includes febrile bone marrow aplasia and febrile neutropenia.] | 49 (73%) | 49 (73%)
Cardiac disorders | -- | --
Tachycardia [Tachycardia includes sinus tachycardia and tachycardia.] | 10 (15%) | 0
Eye disorders | -- | --
Vision blurred | 7 (10%) | 0
Gastrointestinal disorders | -- | --
Mucositis [Mucositis includes anal inflammation, colitis, gastrointestinal inflammation, mucosal inflammation, proctitis, and stomatitis.] [Encompasses more than one system organ class.] | 62 (92%) | 34 (51%)
Nausea | 56 (84%) | 17 (25%)
Vomiting | 51 (76%) | 12 (18%)
Abdominal pain [Abdominal pain includes abdominal discomfort, abdominal pain, and abdominal pain upper.] | 30 (45%) | 2 (3%)
Constipation | 28 (42%) | 0
Diarrhea | 19 (28%) | 1 (1%)
General disorders and administration site conditions | -- | --
Pyrexia | 24 (36%) | 3 (4%)
Injury, poisoning and procedural complications | -- | --
Transfusion reaction [Transfusion reaction includes allergic transfusion reaction and anaphylactic transfusion reaction.] | 8 (12%) | 2 (3%)
Metabolism and nutrition disorders | -- | --
Decreased appetite | 43 (64%) | 27 (40%)
Nervous system disorders | -- | --
Headache | 19 (28%) | 0
Anxiety [Anxiety includes akathisia, agitation, anxiety, and irritability.] | 10 (15%) | 0
Respiratory, thoracic, and mediastinal disorders | -- | --
Epistaxis | 13 (19%) | 5 (7%)
Oropharyngeal pain [Oropharyngeal pain includes mouth ulceration, oral pain, and oropharyngeal pain.] | 12 (18%) | 3 (4%)
Cough | 7 (10%) | 0
Skin and subcutaneous tissue disorders | -- | --
Alopecia | 48 (72%) | 1 (1%)
Rash [Rash includes rash, rash erythematous, rash maculo-papular, and urticaria.] | 14 (21%) | 0
Pruritus [Pruritus includes anal pruritus, pruritus, and pruritus allergic.] | 13 (19%) | 0
Skin hyperpigmentation | 12 (18%) | 0
Vascular disorders | -- | --
Hypertension | 8 (12%) | 1 (1%)

Hematologic Malignancy

As of July 2025, hematologic malignancies have been diagnosed in 10/67 (15%) clinical study patients [see Warnings and Precautions (5.1)]. At diagnosis of hematologic malignancy, all 10 patients had predominant integrations; 7 in proto-oncogenes, including 6 in MECOM. Pathological diagnoses ranged between myelodysplastic syndrome (MDS)-unilineage dysplasia to acute myeloid leukemia. As of July 2025, 9 of the 10 patients had received allogeneic hematopoietic stem cell transplant. One of the patients with MDS relapsed 6 months after an allogeneic transplant and required re-treatment of MDS.

Serious Infections

Important opportunistic infections that have been diagnosed within the first 3 months after treatment with SKYSONA include BK cystitis, cytomegalovirus reactivation, human herpesvirus-6 viremia, candidiasis, and bacteremias. Opportunistic infections after the first 3 months include an atypical mycobacterium vascular device infection, pseudomonas bacteremia, and Epstein-Barr virus reactivations diagnosed as late as 18 months after treatment with SKYSONA. Serious infections involving adenovirus include a case of transverse myelitis at 6 months that was attributed to adenovirus and entero/rhinovirus infection, and a fatal adenovirus infection at 21 months in a patient with CALD progression who developed multisystem organ failure.

Grade 3 or higher infections occurred in 21% of all patients (12% bacterial, 3% viral, and 6% unspecified). The most common Grade 3 or higher infections were vascular device infections (7% of patients) diagnosed as late as 6 months after treatment with SKYSONA, and bacteremias (6% of patients) diagnosed as late as 8 months after treatment with SKYSONA.

Table 2: Grade 3 or 4 Laboratory Abnormalities Occurring in ≥ 40% of Patients Between the Start of Conditioning and 24 Months Following Treatment with SKYSONA [Includes laboratory abnormalities associated with conditioning.]
Laboratory Abnormality | Grade 3 or 4 n (%)
Leukopenia | 67 (100%)
Lymphopenia | 67 (100%)
Thrombocytopenia | 67 (100%)
Neutropenia | 64 (96%)
Anemia | 56 (84%)
Hypokalemia | 28 (42%)

Cytopenias

Grade 3 or higher cytopenias on or after Day 60 following SKYSONA infusion occurred in 47% of patients and included low platelet count (14%), low neutrophil count (22%), low lymphocyte count (27%), and low hemoglobin (2%). Grade 3 cytopenias persisted beyond Day 100 in 15% of patients and included low platelet count (7%), low neutrophil count (9%), and low lymphocyte count (6%).

Serious adverse reactions of pancytopenia occurred in two patients who required support with blood and platelet transfusions as well as growth factors (G-CSF for up to 6 months and eltrombopag for up to 14 months) after SKYSONA administration. One patient had intercurrent parvovirus infection and his pancytopenia was ongoing at least two years after SKYSONA administration. Pancytopenia in the other patient was ongoing until he was diagnosed with myelodysplastic syndrome approximately two years after SKYSONA administration.

Platelet Engraftment Delay

Platelet engraftment was defined as 3 consecutive platelet values ≥ 20 × 10^9/L on different days and no platelet transfusions administered for 7 days immediately preceding and during the evaluation period. Platelet engraftment was not achieved by Day 43 after SKYSONA administration in 13 of 63 patients (21%). Patients treated with SKYSONA achieved platelet engraftment at median (min, max) Day 29 (14, 108) in clinical studies, including two patients treated with a thrombopoietin receptor agonist at the time engraftment criteria were met until 10 or 14 months after treatment with SKYSONA. One of the two had persistence of mild thrombocytopenia after discontinuation of the eltrombopag, and the other remained severely thrombocytopenic (platelet count < 50 × 10^9/L) until he was diagnosed with myelodysplastic syndrome approximately 2 years after SKYSONA administration [see Warnings and Precautions (5.4)].

Neutrophil Engraftment

Neutrophil engraftment was defined as achieving 3 consecutive absolute neutrophil counts (ANC) ≥ 0.5 × 10^9 cells/L (after initial post-infusion nadir) obtained on different days by Day 43 after SKYSONA infusion. While all patients met criteria for neutrophil engraftment following treatment with SKYSONA in clinical trials, 7 of 67 patients (10%) required G-CSF beyond Day 43, including 3 patients who required G-CSF more than 3 months after treatment with SKYSONA. In three other patients, G-CSF discontinuation was followed by a decrease in neutrophil count to < 0.5 × 10^9 cells/L occurring within 3 days and lasting for two to five weeks [see Warnings and Precautions (5.5)].

Infusion-Related Reactions

Nausea and vomiting have occurred on the day of infusion. Premedication with anti-emetic, anti-pyretics and/or antihistamines may be considered.

7 DRUG INTERACTIONS

7.1 Vaccines

The safety and effectiveness of vaccination during or following SKYSONA treatment have not been studied. Vaccination is not recommended during the 6 weeks preceding the start of myeloablative conditioning, and until hematological recovery following treatment with SKYSONA. Where feasible, administer childhood vaccinations prior to myeloablative conditioning for SKYSONA.

7.2 Anti-retrovirals

Patients should not take anti-retroviral medications for at least one month prior to initiating medications for stem cell mobilization and for the expected duration for elimination of the medications, and until all cycles of apheresis are completed [see Warnings and Precautions (5.5)].

Anti-retroviral medications may interfere with SKYSONA manufacture.

8 USE IN SPECIFIC POPULATIONS

8.1 Pregnancy

Risk Summary

There are no available data with SKYSONA administration in pregnant women. Consider the risks associated with mobilization and conditioning agents on pregnancy and fertility.

No animal reproductive and developmental toxicity studies have been conducted to assess whether SKYSONA can cause fetal harm when administered to a pregnant woman.

No nonclinical germline transmission studies have been conducted with SKYSONA.

In the U.S. general population, the estimated background risk of major birth defects and miscarriage in clinically recognized pregnancies is 2% to 4% and 15% to 20%, respectively.

8.2 Lactation

Risk Summary

There is no information regarding the presence of SKYSONA in human milk, the effect on the breastfed infant, and the effects on milk production.

8.3 Females and Males of Reproductive Potential

Contraception

Consult the Prescribing Information of the mobilization and conditioning agents for information on the need for effective contraception.

There are insufficient exposure data to provide a precise recommendation on duration of contraception following treatment with SKYSONA. Males capable of fathering a child and their female partners of childbearing potential should use an effective method of contraception (intra-uterine device or combination of hormonal and barrier contraception) from start of mobilization through at least 6 months after administration of SKYSONA.

Infertility

There are no data on the effects of SKYSONA on fertility.

Data are available on the risk of infertility with myeloablative conditioning. Advise patients of the option to cryopreserve semen before treatment if appropriate.

8.4 Pediatric Use

The safety and efficacy of SKYSONA in children less than 4 years of age have not been established. No data are available [see Clinical Studies (14)].

8.6 Patients with a Full ABCD1 Gene Deletion

In the only patient in the SKYSONA clinical studies who had a full ABCD1 deletion, disease progression occurred. The patient experienced radiologic disease progression in the setting of declining peripheral blood vector copy number, suggesting loss of product efficacy which may have been immune mediated. The patient was subsequently treated with allogeneic hematopoietic stem cell transplant.

8.7 Renal Impairment

SKYSONA has not been studied in patients with renal impairment. Patients should be assessed for renal impairment to ensure hematopoietic stem cell (HSC) transplantation is appropriate.

8.8 Hepatic Impairment

SKYSONA has not been studied in patients with hepatic impairment. Patients should be assessed for hepatic impairment to ensure HSC transplantation is appropriate.

8.9 Patients Seropositive for Human Immunodeficiency Virus (HIV)

SKYSONA has not been studied in patients with HIV-1, HIV-2, HTLV-1, or HTLV-2. A negative serology test for HIV is necessary to ensure acceptance of apheresis material for SKYSONA manufacturing. Apheresis material from patients with a positive test for HIV will not be accepted for SKYSONA manufacturing.

11 DESCRIPTION

SKYSONA (elivaldogene autotemcel) is an autologous HSC-based gene therapy prepared from the patient's HSCs, which are collected via apheresis procedure(s). The autologous cells are enriched for CD34+ cells, then transduced ex vivo with Lenti-D LVV, and cultured with growth factors overnight. Lenti-D LVV is a replication-incompetent, self-inactivating LVV carrying ABCD1 cDNA that encodes normal ALDP. The ABCD1 gene is under the control of an internal MNDU3 promoter, which is a modified viral promoter and has been shown to control expression of the transgene in HSCs and their progeny in all lineages.

The transduced CD34+ cells are washed, formulated into a suspension, and then cryopreserved. SKYSONA is frozen in a patient-specific infusion bag(s) and is thawed prior to administration [see Dosage and Administration (2.1), How Supplied/Storage and Handling (16)]. The thawed product is colorless to white to red, including shades of white or pink, light yellow, and orange suspension of cells and may contain small proteinaceous particles. Due to the presence of cells, the solution may be clear to slightly cloudy and may contain visible cell aggregates.

The formulation contains 5% dimethyl sulfoxide (DMSO).

12 CLINICAL PHARMACOLOGY

12.1 Mechanism of Action

SKYSONA adds functional copies of the ABCD1 cDNA into patients' hematopoietic stem cells (HSCs) through transduction of autologous CD34+ cells with Lenti-D LVV. After SKYSONA infusion, transduced CD34+ HSCs engraft in the bone marrow and differentiate into various cell types, including monocytes (CD14^+) capable of producing functional ALDP. Functional ALDP can then participate in the local degradation of very long chain fatty acids (VLCFAs), which is believed to slow or possibly prevent further inflammation and demyelination.

12.2 Pharmacodynamics

All patients who received SKYSONA with at least 1 month of follow-up produced ALDP in CD14^+ cells (N=23, Study 1; N=31, Study 2), demonstrating early expression of the transgene. The %ALDP+ cell counts stabilized at 6 months after SKYSONA infusion. Patients had a Month 6 median (min, max) %ALDP+ CD14^+ cells of 16% (2%, 71%) in Study 1 (N=23) and 26% (2%, 86%) in Study 2 (N=25).

In peripheral blood, the %ALDP+ CD14^+ cells remained generally stable through Month 24 with a median (min, max) of 15% (6%, 45%) in Study 1 (N=23) and 28% (2%, 40%) in Study 2 (N=11). ALDP expression was quantifiable in 43% of the patients who had follow-up through Month 60 in Study 1 (N=7), indicating long-term expression of transgenic ALDP in the progeny of hematopoietic stem cells.

12.3 Pharmacokinetics

SKYSONA is an autologous gene therapy which includes HSCs that have been genetically modified ex vivo. The nature of SKYSONA is such that conventional studies on pharmacokinetics, absorption, distribution, metabolism, and elimination are not applicable.

13 NONCLINICAL TOXICOLOGY

13.1 Carcinogenesis, Mutagenesis, Impairment of Fertility

No carcinogenicity studies have been performed with SKYSONA. No studies have been conducted to evaluate the effects of SKYSONA on fertility.

14 CLINICAL STUDIES

The safety and efficacy of SKYSONA were assessed in two 24-month, open-label, single-arm studies in patients with early, active CALD as defined by Loes score between 0.5 and 9 (inclusive) and gadolinium enhancement (GdE+) on MRI, as well as a neurologic function score (NFS) of ≤ 1, indicating limited changes in neurologic function. The NFS was used to evaluate 15 domains of neurological function with a maximum score of 25. A total NFS=0 indicates absence of neurologic dysfunction or asymptomatic disease. The patients enrolled and treated with SKYSONA (Study 1, N=32; Study 2, N=35) all had elevated very long chain fatty acid (VLCFA) levels and confirmed mutations in the ABCD1 gene. Following completion of Study 1 and Study 2, patients enroll in a subsequent and ongoing long-term follow-up study. The efficacy of SKYSONA was compared to an external untreated natural history control. Data for the Natural History Population in the retrospective natural history study (Study 3) was collected from existing medical records for patients with CALD. The Natural History Population had early, active disease at diagnosis, though gadolinium status was defined by either having a GdE+ MRI during the study or unknown GdE status and clinical course that suggested active disease.

SKYSONA Studies

Study 1 is complete and Study 2 is ongoing at the time of product approval. In Study 1, patients were 47% White/Caucasian, 38% Hispanic, 3% Asian, 3% Black or African American, and 16% other races including mixed race. In Study 2, patients were 60% White/Caucasian, 14% Hispanic, 6% Black or African American, 6% other races including mixed race.

Mobilization and Apheresis:

- G-CSF 10 µg/kg (median) for a minimum of 4 days
- Plerixafor 0.24 mg/kg for up to 3 days – optional in Study 1 (administered to 34% of patients) and required in Study 2

For all patients, one cycle of mobilization and apheresis and one to two apheresis collection days were sufficient to obtain the requisite number of cells needed for manufacturing.

Pre-treatment Myeloablative Conditioning:

- Study 1: Busulfan dose median (min, max) 14 (11.2 to 16.8) mg/kg over 4 days
- Study 2: Busulfan dose median (min, max) 16.8 (12 to 21.2) mg/kg over 4 days

Pre-treatment Lymphodepletion:

- Study 1: Cyclophosphamide dose median (min, max) 199 (151 to 213) mg/kg over 4 days
- Study 2: Fludarabine dose 180 mg/m^2 over 6 days for 11 patients; 160 mg/m^2 over 4 days (actual dose range 122 to 196 mg/m^2) for 24 patients; (fludarabine dose decreased due to viral infections in the initial cohort)

Patients received seizure, hepatic veno-occlusive disease, anti-fungal, and antibiotic prophylaxis in accordance with institutional guidelines.

SKYSONA Administration:

- All patients were administered SKYSONA as an intravenous infusion with a median (min, max) dose of 12 × 10^6 (5, 38.2) CD34+ cells/kg (N=67).

After SKYSONA Administration:

- G-CSF – optional in Study 1 (administered to 75% of patients) and required in Study 2 (beginning on Day 5)
- See Section 6 for engraftment information.

Comparison of SKYSONA with the Natural History of CALD

A post-hoc enrichment analysis in symptomatic patients compared time from onset of symptoms (NFS ≥ 1) to time to first Major Functional Disability (MFD) or death (i.e., MFD-free survival) in SKYSONA treated and Natural History patients. The MFDs are defined as: loss of communication, cortical blindness, requirement for tube feeding, total incontinence, wheelchair dependence, or complete loss of voluntary movement. To be included in the analysis, patients had to have symptoms at baseline (NFS=1) or be asymptomatic (NFS=0) at baseline and have developed symptoms (NFS ≥ 1) during the course of follow-up in the study. Additionally, they had to have at least 24 months of follow-up after initial NFS ≥ 1 or have had an event (MFD or death).

The 7 patients in the Natural History Population were a median (min, max) 9 (5, 15) years old at time of CALD diagnosis, and 10 (5, 17) years at time of first NFS ≥ 1. The median Loes score at diagnosis was 5 (2, 9). Four (57%) had a baseline brain MRI pattern of disease inclusive of parieto-occipital involvement, 2 (29%) had frontal disease (without parieto-occipital involvement) and 1 (14%) had isolated pyramidal tract disease. One (14%) had a baseline NFS=1 at diagnosis, and the remainder were asymptomatic (NFS=0) at diagnosis.

The symptomatic SKYSONA subpopulation (N=11) had baseline median (min, max) age at treatment of 6 (4, 10) years, age at first NFS ≥ 1 of 7 (4, 10) years, and a baseline Loes score of 2.5 (1, 9). Ten (91%) patients had a parieto-occipital pattern of disease on brain MRI and 1 (9%) had isolated pyramidal tract disease. At baseline, 2 (18%) patients had an NFS=1 and the remainder were asymptomatic (NFS=0) prior to treatment.

Slower progression to MFD or death from time of symptom onset (first NFS ≥ 1) was seen for early, active CALD patients treated with SKYSONA compared to a similar natural history of disease (Figure 1). Kaplan-Meier (KM) estimated MFD-free survival at Month 24 from time of first NFS ≥ 1 were 72% (95% CI: 35%, 90%) for the symptomatic SKYSONA subpopulation and 43% (95% CI: 10%, 73%) for the Natural History Population. There were insufficient data beyond 24 months for the symptomatic SKYSONA subpopulation to assess long-term MFD-free survival as compared to the natural history of disease. There was insufficient duration of follow-up to assess efficacy in SKYSONA treated patients who remained asymptomatic.

Figure 1 Kaplan-Meier Curve of MFD-free Survival in Symptomatic Patients of SKYSONA and Natural History Populations

Isolated Pyramidal Tract Disease

Two untreated patients in Study 3 had early CALD with isolated pyramidal tract disease on brain MRI. Both remained asymptomatic for approximately 10 years following CALD diagnosis with first symptoms documented at 19 and 20 years of age. Ten patients with early, active pyramidal tract disease were treated with SKYSONA in Studies 1 and 2, and have only been followed a maximum of 77 months following treatment and to a maximum age at last follow-up of 15 years. Two (20%) SKYSONA-treated patients were diagnosed with myelodysplastic syndrome (MDS) and received allo-HSCT as treatment of the hematologic malignancy. One (10%) patient developed symptoms and worsening lesions on brain MRI approximately 6 months following treatment with SKYSONA and was withdrawn from the study to receive allo-HSCT at the investigator's discretion. He subsequently died of transplant-related causes.

Comparison of SKYSONA with Allogeneic Hematopoietic Stem Cell Transplant (allo-HSCT)

There were insufficient data to compare relative efficacy of SKYSONA to the standard of care, allogeneic hematopoietic stem cell transplant (allo-HSCT) in the treatment of CALD. However, while it does not inform the efficacy analysis, comparison of SKYSONA with an external allo-HSCT control (pooled from Study 3 and from a mixed prospective and retrospective allo-HSCT data collection study, Study 4) was performed for overall survival (OS) due to concerns about treatment-related toxicities. OS was analyzed as time-to-event Kaplan-Meier estimates comparing SKYSONA (entire efficacy population, N=61) to early, active allo-HSCT subpopulations by donor type: human leukocyte antigen (HLA)-Matched allo-HSCT Subpopulation (N=34) and HLA-Mismatched allo-HSCT Subpopulation (N=17) (Figure 2). There were insufficient long-term data to compare OS beyond Month 24. However, a distinct difference in OS in the first 9 months following treatment was seen for the subpopulation who received allo-HSCT from an HLA-mismatched donor as compared to SKYSONA and allo-HSCT from an HLA-matched donor. While this analysis does not provide evidence of efficacy of SKYSONA, it does demonstrate a survival advantage of SKYSONA as compared to allo-HSCT from an HLA-mismatched donor, with early mortality in the HLA-mismatched allo-HSCT Subpopulation largely attributed to allo-HSCT-related toxicities.

No patient experienced acute (≥ Grade II) or chronic graft versus host disease (GVHD) after SKYSONA treatment.

Figure 2 Kaplan-Meier Curve of Overall Survival Between SKYSONA and Allo-HSCT Treated Populations

Post-treatment Brain MRI

At Month 24 following treatment with SKYSONA, 7/36 (19%) evaluable patients had a cerebral MRI Loes score increase of ≥ 6 points; 3/30 (10%) evaluable allo-HSCT patients had a cerebral MRI Loes score increase of ≥ 6 points.

16 HOW SUPPLIED/STORAGE AND HANDLING

SKYSONA is supplied in one or two infusion bags containing a frozen suspension of genetically modified autologous cells enriched for CD34+ cells. Each bag contains approximately 20 mL. Each SKYSONA infusion bag is individually packed within an overwrap in a metal cassette. SKYSONA is shipped from the manufacturing facility to the infusion center in a cryoshipper, which may contain multiple metal cassettes intended for treatment of a single patient. A Lot Information Sheet is affixed inside the shipper.

- 20 mL infusion bag, overwrap, and metal cassette (NDC 73554-2111-1)

STORAGE AND HANDLING

Match the identity of the patient with the patient identifiers on the metal cassette(s), infusion bag(s), and Lot Information Sheet upon receipt.

- Store SKYSONA frozen in the vapor phase of liquid nitrogen at less than or equal to -140°C (-220°F) until ready for thaw and administration.
- Thaw SKYSONA prior to infusion [see Dosage and Administration (2)].
- Do not re-freeze after thawing.
- Do not irradiate SKYSONA as this could lead to inactivation.

17 PATIENT COUNSELING INFORMATION

Advise the patient and their caregiver(s) to read the FDA-approved patient labeling (Medication Guide).

Discuss the following with the patient and their caregiver(s):

Hematologic Malignancy

Inform the patient and/or caregiver that insertional oncogenesis has been observed and resulted in myelodysplastic syndrome (MDS) and acute myeloid leukemia (AML) in children following treatment with SKYSONA. Inform the patient that these are life-threatening diseases and children have died from complications of treatment for malignancy. Treatment for hematologic malignancies can include chemotherapy and bone marrow transplant. Relapse of MDS or AML may occur which may require retreatment.

Patients treated with SKYSONA will need lifelong monitoring for hematologic malignancies via blood tests. Advise patients that they may require more frequent blood tests and invasive bone marrow biopsies if routine blood test results are concerning for the development of malignancy [see Warnings and Precautions (5.1)]. Advise the patient and/or caregiver to seek attention for any signs or symptoms of malignancy, such as fatigue or easy bleeding or bruising, and advise the patient to contact bluebird bio at 1-833-999-6378 if they are diagnosed with a hematologic malignancy.

Efficacy Failure

Inform the patient and/or caregiver that there has been unexplained efficacy failure after treatment with SKYSONA [see Use in Specific Populations (8.6)].

Need for Allogeneic Hematopoietic Stem Cell Transplant

Inform the patient that some patients have required an allogeneic hematopoietic stem cell transplant after treatment with SKYSONA, in order to treat efficacy failure or hematologic malignancy. Advise the patients that they will be monitored for these complications [see Warnings and Precautions (5.1)].

Serious Infections

Inform the patient that severe infections, including life-threatening infections, have occurred following SKYSONA treatment and may require prolonged hospitalization [see Warnings and Precautions (5.2)].

Prolonged Cytopenias

Inform the patient and/or caregiver that prolonged cytopenias have been observed following SKYSONA treatment and that they may require frequent blood draws until blood counts have returned to safe levels. Advise the patient and/or caregiver to seek attention for any signs or symptoms of thrombocytopenia, neutropenia, or anemia, such as easy bleeding, serious infections, or fatigue [see Warnings and Precautions (5.3)].

Delayed Platelet Engraftment

Inform the patient that a risk of bleeding and a likely need for platelet transfusion exists after myeloablative conditioning and during the weeks to months before platelet engraftment occurs [see Warnings and Precautions (5.4)].

Risk of Neutrophil Engraftment Failure

Inform the patient and/or caregiver of the potential risk of neutrophil engraftment failure and the need for rescue treatment with their back-up collection of CD34+ cells, if engraftment failure occurs [see Warnings and Precautions (5.5)].

Laboratory Test Interference

Advise patients that they may test positive for HIV if tested using a PCR test after being treated with SKYSONA [see Warnings and Precautions (5.8)]. Advise the patient and/or caregiver that they should notify any healthcare provider about this possibility prior to being tested for HIV.

Manufacturing Failure

Ensure that the patient and/or caregiver understands the risk of manufacturing failure. In case of manufacturing failure or the need for additional cells, additional cell collection and manufacturing of SKYSONA may be needed [see Dosage and Administration (2.2)].

Advise patients that they will be screened for HBV, HCV, HIV, and HTLV before collection of cells [see Dosage and Administration (2.2)].

Inform patients that they should not donate blood, organs, tissues, or cells at any time in the future [see Dosage and Administration (2.3)].

Manufactured for:
bluebird bio, Inc.
Somerville, MA 02145

US License No 2160

SKYSONA and LENTI-D are trademarks of bluebird bio, Inc
© bluebird bio, Inc. 2025. All rights reserved.

MEDICATION GUIDE
SKYSONA® (pronounced sky-SO-nuh)
(elivaldogene autotemcel)

What is the most important information I or my caregiver should know about SKYSONA?
SKYSONA may cause cancer of the blood and bone marrow, which can be life-threatening and lead to death. Blood cancer has resulted from treatment with SKYSONA because cancer-causing genes have been turned on by the gene therapy. Patients have developed cancer as early as one year after SKYSONA administration, prior to SKYSONA having time to potentially help their CALD. Blood cancer can also take years to develop, and has been diagnosed more than 9 years later. The percent of patients who will develop cancer and the maximum timeframe when cancer caused by SKYSONA could develop is unknown. Blood cancer is usually treated with chemotherapy and may require stem cell transplant. Stem cell transplant using cells from a donor have been used to treat children diagnosed with blood cancer that was caused by SKYSONA.
Blood cancers, including those following SKYSONA treatment, will lead to death if not treated. Cancer may recur and require further treatment. Treatment of blood cancer has led to death due to complications. Because of the risk of cancer caused by SKYSONA, your doctor may recommend that you are evaluated by a hematologist to determine if you have underlying risk factors that could further increase your risk for cancer and change whether SKYSONA is appropriate for you.
Before you are treated with SKYSONA, you should have a detailed discussion with your doctor about the risks and benefits of SKYSONA and alternative treatment options. Alternative treatment may include an allogeneic hematopoietic stem cell transplant. Discuss with your physician the possibility of a stem cell transplant using cells from a suitable donor if one is available.
Because of the risk of cancer, it is important for you to be monitored lifelong. At a minimum we recommend blood tests every 3 months for 15 years. Blood tests will look at your blood cell counts and the locations in your blood cells where the gene therapy is inserted. If your blood counts are too low or too high, or if you have lots of cells with the same gene therapy insertion sites, additional testing may be recommended. Additional testing might include more frequent blood tests to watch you more closely for changes in your blood. Additional testing could also include a bone marrow evaluation, which can tell your doctor more than blood tests about the health of your bone marrow and if there is cancer forming.
If blood cancer develops quickly or if you have not been having the recommended blood or bone marrow tests, you might experience symptoms of cancer before it is diagnosed. You or your caregiver should call your healthcare provider right away for any of these signs or symptoms:

- Abnormal bruising or bleeding (including nosebleed)
- Blood in urine, stool, or vomit
- Coughing up blood
- Severe headache
- Unusual stomach or back pain
- Fever (100.4°F/38°C or higher)
- Swollen glands
- Abnormal tiredness

If you are diagnosed with a cancer, have your treating physician contact bluebird bio at 1-833-999-6378.
SKYSONA may cause life-threatening allergic reactions as it contains DMSO, a commonly used preserving agent. Please inform your healthcare provider if you have been told that your child has a DMSO allergy or has experienced a reaction after receiving a DMSO-containing product.
It is important that you or your caregiver tell your healthcare providers that you have received SKYSONA.

What is SKYSONA?
SKYSONA is a one-time gene therapy to treat boys with early, active cerebral adrenoleukodystrophy (CALD). CALD is a genetic disease caused by mutations in the ABCD1 gene that lead to the buildup of very long chain fatty acids (VLCFAs) in the brain. These VLCFAs may destroy the protective covering around nerve cells and cause damage to the brain. Once this occurs, this damage can be seen on magnetic resonance imaging (MRI) of the brain, which is when the cerebral form of adrenoleukodystrophy (CALD) is diagnosed. SKYSONA may be recommended if this damage is determined to be early (based on a lesser degree of the damage on MRI) and if cerebral disease is active (based on presence of contrast enhancement on MRI that indicates this damage is ongoing). SKYSONA is made specifically for each patient, using the patient's own blood stem cells and adds functional copies of the ABCD1 gene to your cells. This may help your body to break down the VLCFAs to slow the progression of damage to the brain and slow the decline in neurologic function.

How will I get SKYSONA?
Before treatment: Your healthcare providers will give you other medicines, including chemotherapy medicine, as part of your treatment before you are given SKYSONA. It's important that you or your caregiver talk to your healthcare providers about the risks and benefits of all medicines involved in your treatment.
After receiving the chemotherapy, it may not be possible for you to father a child. You or your caregiver should consider discussing options for fertility preservation with your doctor before treatment.
STEP 1: SKYSONA is made specifically for you from your own blood stem cells. Your healthcare provider will collect your blood stem cells through a process called mobilization and apheresis (A-feh-REE-sis). This process takes approximately one week.
'Back-up' stem cells (or 'rescue cells') are also collected and stored at the hospital. This is a precaution in case there is a problem during the treatment process. If this happens, your back-up stem cells will be given back to you. If you receive back-up cells, you will have no benefit from SKYSONA.
STEP 2: Your blood stem cells will be sent to a manufacturing site where they are used to make SKYSONA. It takes approximately 51 – 65 days from the time your cells are collected to make and test SKYSONA before it is shipped to your healthcare providers, but the time may vary.
STEP 3: Before you receive SKYSONA, your healthcare providers will give you chemotherapy for a few days to make room in the bone marrow. You will be admitted to the hospital for this step and remain in the hospital until after SKYSONA infusion.
STEP 4: SKYSONA is given by an intravenous infusion (into your vein). You may receive one or two bags of SKYSONA. Each bag is infused in less than 60 minutes.
After SKYSONA infusion, you may stay in the hospital for up to approximately 2 months so that your healthcare team can closely monitor your recovery. Your healthcare providers will determine when you can go home.

What should I avoid after receiving SKYSONA?

- Do not donate blood, organs, tissues or cells.

What are the possible or reasonably likely side effects of SKYSONA?
There is a risk of blood cancer following treatment with SKYSONA which will require lifelong monitoring. You will be monitored at least every 3 months for a minimum of 15 years for this.
Possible or reasonably likely side effects when treated with SKYSONA are:

- While receiving chemotherapy to prepare your body for SKYSONA:
  - Nausea, vomiting, decreased appetite, constipation, abdominal pain
  - Headache
  - Rash
- On the day of treatment with SKYSONA
  - Life-threatening allergic reaction
  - Nausea, vomiting
- Following treatment
  - Blood cancer. Refer to "What is the most important information I or my caregiver should know about SKYSONA?"
  - Low blood counts leading to a risk of bleeding and/or infection. Until your blood counts (platelets, white blood cells, red blood cells) return to safe levels, you may be treated with blood and platelet transfusions and other medicines that prevent bleeding and infection by increasing your blood counts. Most patients' blood counts return to safe levels in about one month after treatment with SKYSONA. Some patients' blood counts may not recover for > 1 year. Tell your healthcare provider right away if you get a fever, are feeling tired, or have easy bleeding or bruising.
  - Life-threatening infections. Patients treated with SKYSONA may experience serious or life-threatening infections, including infections of the bloodstream by bacteria or viruses. Infections often occur in the first 1 or 2 months after treatment with SKYSONA, but can occur > 1 year later. Tell your healthcare provider right away if you develop fever, chills, or any signs or symptoms of an infection.
  - Inflamed and painful mouth (this typically occurs during the first 2 months after SKYSONA treatment)
  - Nausea, vomiting, decreased appetite, constipation, abdominal pain, diarrhea
  - Headache
  - New onset seizures

These are not all the possible side effects of SKYSONA. Your healthcare providers may give you other medicines to treat your side effects. Call your doctor for medical advice about side effects. You may report side effects to the FDA at 1-800-FDA-1088 or to bluebird bio at 1-833-999-6378.

General information about the safe and effective use of SKYSONA.
Because of the risk of blood cancer, it is important for you to be monitored lifelong. At a minimum we recommend blood tests every 3 months for 15 years.
SKYSONA treatment failures have been reported and progression of CALD may occur. After treatment with SKYSONA you will need to continue to follow-up with your doctor who will monitor you for any clinical and radiographic worsening of CALD.
Treatment with SKYSONA may cause a false-positive human immunodeficiency virus (HIV) test result by some commercial tests. If you need to have an HIV test, talk with your healthcare provider about the appropriate test to use.
Medicines are sometimes prescribed for purposes other than those listed in a Medication Guide. Talk to your healthcare provider about any concerns. You can ask your healthcare provider for information about SKYSONA that is written for healthcare professionals.
For more information, go to SKYSONA.com or call 1-833-666-2583 for bluebird Patient Services (my bluebird support).
Manufactured for and distributed by: bluebird bio, Inc., Somerville, Massachusetts 02145

This Medication Guide has been approved by the U.S. Food and Drug Administration.
Issued: August 2025

PRINCIPAL DISPLAY PANEL - 20 mL Bag Patient Identifier Label

elivaldogene autotemcel
skysona™

Suspension for IV infusion
20 mL containing 4 to 30 x 10^6 cells/mL
(3.6 to 30 x 10^6 CD34+ cells/mL)

Confirm Patient Identifiers

Last Name: $LastName$

First Name: $FirstName$

Date of Birth: $DOB$

bbb Patient ID: $bbb_PatientID$

COI ID: $bbb_COI_ID$

LOT: $LOT$

EXP: $Expiry$

Bag X of X

DIN: $DIN1_DIN2$

U.S. Lic. # 2160

Label P/N: XXXXXXX

bluebirdbio®

PRINCIPAL DISPLAY PANEL - 20 mL Bag Label

elivaldogene autotemcel
skysona™

Suspension for IV infusion
20 mL containing 4 to 30 x 10^6 cells/mL
(3.6 to 30 x 10^6 CD34+ cells/mL)

For autologous use only. For intravenous use only. Rx only.

Contains genetically modified autologous hematopoietic stem cells
suspended in cryopreservation solution containing 5% DMSO.

Not evaluated for infectious substances.

Do not irradiate. Do not use an in-line blood filter or infusion pump.

See full prescribing information for dosage and administration.

See Lot Information Sheet for number of infusion bags and
CD34+ cells per kg for this patient. Dispense with Medication Guide.

P/N: XXXXXXX
Label P/N: XXXXXXX

Manufactured for: bluebird bio, Inc.
Somerville, MA 02145

PRINCIPAL DISPLAY PANEL - 20 mL Bag Cassette Label

elivaldogene autotemcel
skysona™

Suspension for IV infusion
20 mL containing 4 to 30 x 10^6 cells/mL
(3.6 to 30 x 10^6 CD34+ cells/mL)

For autologous use only. For intravenous use only. Rx only.

Contains autologous hematopoietic stem cells transduced with Lenti-D
lentiviral vector suspended in cryopreservation solution containing 5% DMSO.

Keep infusion bag(s) in the metal cassette(s). Store in the vapor phase of
liquid nitrogen at ≤ -140°C until ready for thaw and administration. Once
thawed do not re-freeze.

See full prescribing information for dosage and administration.

Do not irradiate. Do not use an in-line blood filter or infusion pump.

This medicine contains genetically modified cells.

Not evaluated for infectious substances. No preservatives.

See Lot Information Sheet for number of infusion bags and CD34+ cells
per kg for this patient. Dispense with Medication Guide.

Confirm Patient Identifiers

Last Name: $LastName$

First Name: $FirstName$

Date of Birth: $DOB$

bbb Patient ID: $bbb_PatientID$

COI ID: $bbb_COI_ID$

DIN: $DIN1_DIN2$

LOT: $LOT$

EXP: $Expiry$

Bag X of X

U.S. Lic. # 2160

Manufactured for: bluebird bio, Inc.
Somerville, MA 02145
1-833-999-6378
SKYSONA.com

P/N: XXXXXXX
Label P/N: XXXXXXX

bluebirdbio®